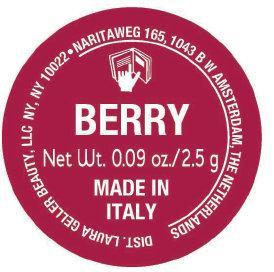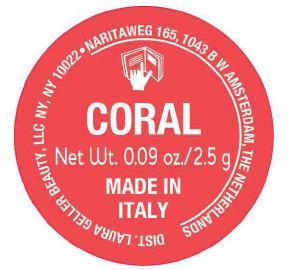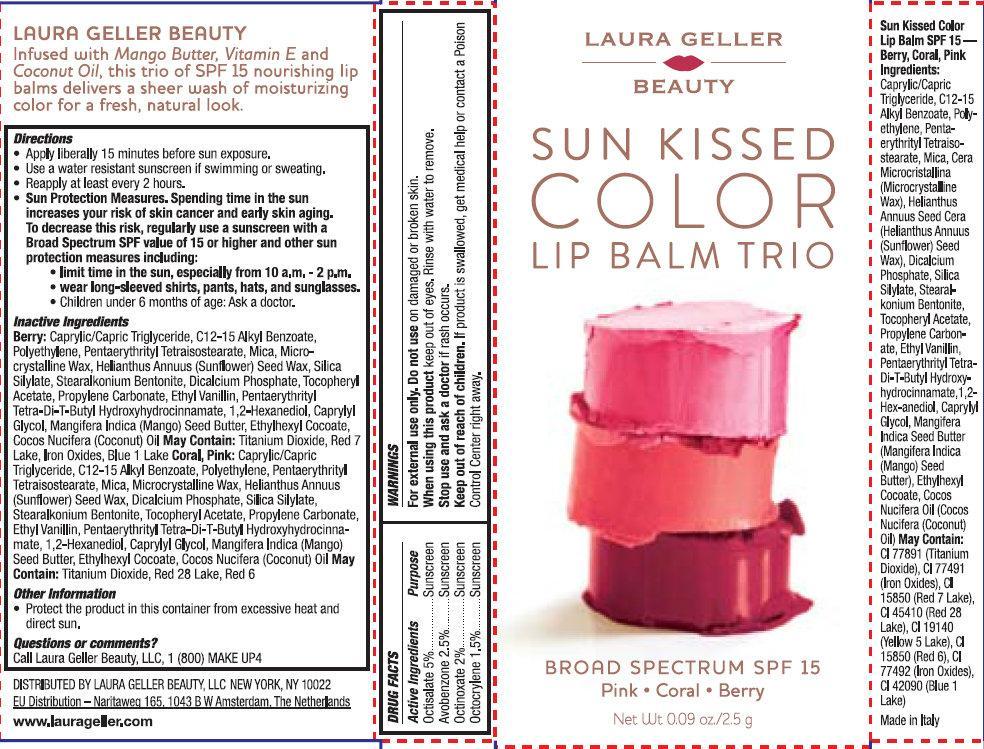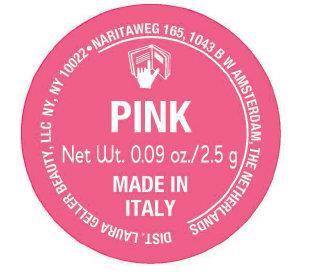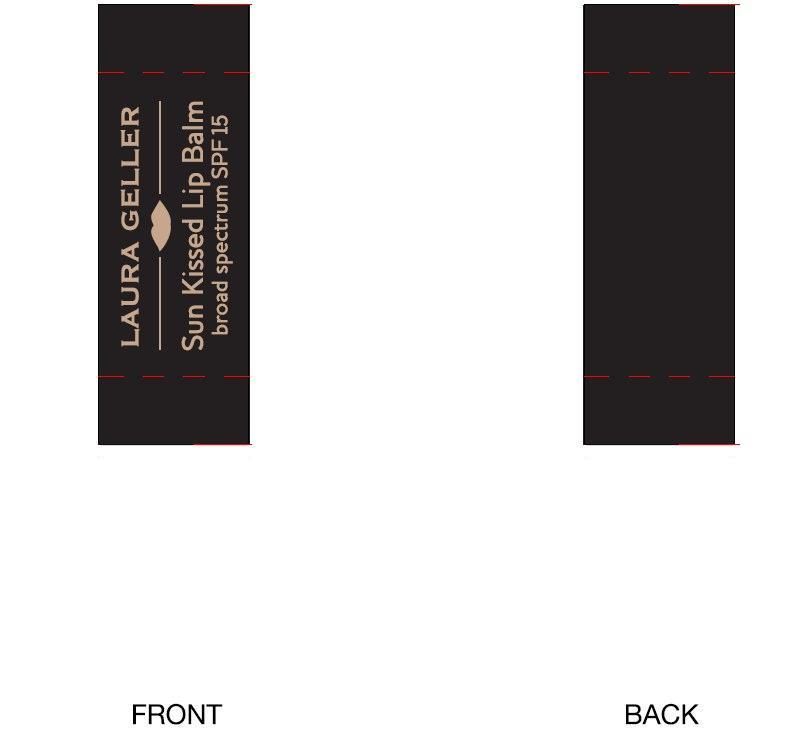 DRUG LABEL: LAURA GELLER BEAUTY SUN KISSED COLOR LIP BALM TRIO BROAD SPECTRUM SPF 15 Pink - Coral - Berry
NDC: 51389-122 | Form: KIT | Route: TOPICAL
Manufacturer: LAURA GELLER MAKE UP INC.
Category: otc | Type: HUMAN OTC DRUG LABEL
Date: 20191226

ACTIVE INGREDIENTS: OCTISALATE 5 g/100 g; AVOBENZONE 2.5 g/100 g; OCTINOXATE 2 g/100 g; OCTOCRYLENE 1.5 g/100 g; OCTISALATE 5 g/100 g; AVOBENZONE 2.5 g/100 g; OCTINOXATE 2 g/100 g; OCTOCRYLENE 1.5 g/100 g; OCTISALATE 5 g/100 g; AVOBENZONE 2.5 g/100 g; OCTINOXATE 2 g/100 g; OCTOCRYLENE 1.5 g/100 g
INACTIVE INGREDIENTS: MEDIUM-CHAIN TRIGLYCERIDES; ALKYL (C12-15) BENZOATE; HIGH DENSITY POLYETHYLENE; PENTAERYTHRITYL TETRAISOSTEARATE; MICA; MICROCRYSTALLINE WAX; HELIANTHUS ANNUUS SEED WAX; CALCIUM PHOSPHATE, DIBASIC, ANHYDROUS; .ALPHA.-TOCOPHEROL ACETATE; PROPYLENE CARBONATE; ETHYL VANILLIN; PENTAERYTHRITOL TETRAKIS(3-(3,5-DI-TERT-BUTYL-4-HYDROXYPHENYL)PROPIONATE); 1,2-HEXANEDIOL; CAPRYLYL GLYCOL; MANGIFERA INDICA SEED BUTTER; ETHYLHEXYL COCOATE; COCONUT OIL; TITANIUM DIOXIDE; D&C RED NO. 28; D&C RED NO. 6; MEDIUM-CHAIN TRIGLYCERIDES; ALKYL (C12-15) BENZOATE; HIGH DENSITY POLYETHYLENE; PENTAERYTHRITYL TETRAISOSTEARATE; MICA; MICROCRYSTALLINE WAX; HELIANTHUS ANNUUS SEED WAX; CALCIUM PHOSPHATE, DIBASIC, ANHYDROUS; .ALPHA.-TOCOPHEROL ACETATE; PROPYLENE CARBONATE; ETHYL VANILLIN; PENTAERYTHRITOL TETRAKIS(3-(3,5-DI-TERT-BUTYL-4-HYDROXYPHENYL)PROPIONATE); 1,2-HEXANEDIOL; CAPRYLYL GLYCOL; MANGIFERA INDICA SEED BUTTER; ETHYLHEXYL COCOATE; COCONUT OIL; TITANIUM DIOXIDE; D&C RED NO. 28; D&C RED NO. 6; MEDIUM-CHAIN TRIGLYCERIDES; ALKYL (C12-15) BENZOATE; HIGH DENSITY POLYETHYLENE; PENTAERYTHRITYL TETRAISOSTEARATE; MICA; MICROCRYSTALLINE WAX; HELIANTHUS ANNUUS SEED WAX; CALCIUM PHOSPHATE, DIBASIC, ANHYDROUS; .ALPHA.-TOCOPHEROL ACETATE; PROPYLENE CARBONATE; ETHYL VANILLIN; PENTAERYTHRITOL TETRAKIS(3-(3,5-DI-TERT-BUTYL-4-HYDROXYPHENYL)PROPIONATE); 1,2-HEXANEDIOL; CAPRYLYL GLYCOL; MANGIFERA INDICA SEED BUTTER; ETHYLHEXYL COCOATE; COCONUT OIL; TITANIUM DIOXIDE; D&C RED NO. 7; FERRIC OXIDE RED; FD&C BLUE NO. 1

LAURA GELLER BEAUTY SUN KISSED COLOR LIP BALM TRIO BROAD SPECTRUM SPF 15 Pink - Coral - Berry

Active Ingredients

Octisalate 5%
Avobenzone 2.5%
Octinoxate 2%
Octocrylene 1.5%

Purpose

Sunscreen

WARNINGS

For external use only.

Do not use

on damaged or broken skin.

When using this product

keep out of eyes. Rinse with water to remove.

Stop use and ask a doctor

if rash occurs.

Keep out of reach of children.

If product is swallowed, get medical help or contact a Poison Control Center right away.

Directions

- Apply liberally 15 minutes before sun exposure.
- Use a water resistant sunscreen if swimming or sweating.
- Reapply at least every 2 hours.
- Sun Protection Measures. Spending time in the sun increases your risk of skin cancer and early skin aging. To decrease this risk, regularly use a sunscreen with a Broad Spectrum SPF value of 15 or higher and other sun protection measures including:
- limit time in the sun, especially from 10 a.m. - 2 p.m.
- wear long-sleeved shirts, pants, hats and sunglasses.
- children under 6 months of age: Ask a doctor.

Inactive Ingredients

Berry: Caprylic/Capric Triglyceride, C12-15 Alkyl Benzoate, Polyethylene, Pentaerythrityl Tetraisostearate, Mica, Microcrystalline Wax, Helianthus Annuus (Sunflower) Seed Wax, Silica Silylate, Stearalkonium Bentonite, Dicalcium Phosphate, Tocopheryl Acetate, Propylene Carbonate, Ethyl Vanillin, Pentaerythrityl Tetra-Di-T-Butyl Hydroxyhydrocinnamate, 1,2-Hexanediol, Caprylyl Glycol, Mangifera Indica (Mango) Seed Butter, Ethylhexyl Cocoate, Cocos Nucifera (Coconut) Oil. May Contain: Titanium Dioxide, Red 7 Lake, Iron Oxides, Blue 1 Lake Coral, Pink: Caprylic/Capric Triglyceride, C12-15 Alkyl Benzoate, Polyethylene, Pentaerythrityl Tetraisostearate, Mica, Microcrystalline Wax, Helianthus Annuus (Sunflower) Seed Wax, Dicalcium Phosphate, Silica Silylate, Stearalkonium Bentonite,
Tocopheryl Acetate, Propylene Carbonate, Ethyl Vanillin, Pentaerythrityl Tetra-Di-T-Butyl Hydroxyhydrocinnamate, 1,2-Hexanediol, Caprylyl Glycol, Mangifera Indica (Mango) Seed Butter, Ethylhexyl Cocoate, Cocos Nucifera (Coconut) Oil. May Contain: Titanium Dioxide, Red 28 Lake, Red 6

Other Information

- Protect the product in this container from excessive heat and direct sun.

Questions or comments?

Call Laura Geller Beauty, LLC, 1 (800) MAKE UP4

LAURA GELLER BEAUTY SUN KISSED COLOR LIP BALM TRIO BROAD SPECTRUM SPF 15 Pink - Coral - Berry (51389-122-03)

LAURA GELLER Sun Kissed Lip Balm broad spectrum SPF 15 PINK 2.5g (51389-123-01)

LAURA GELLER Sun Kissed Lip Balm broad spectrum SPF 15 CORAL 2.5g (51389-124-01)

LAURA GELLER Sun Kissed Lip Balm broad spectrum SPF 15 BERRY 2.5g (51389-125-01)